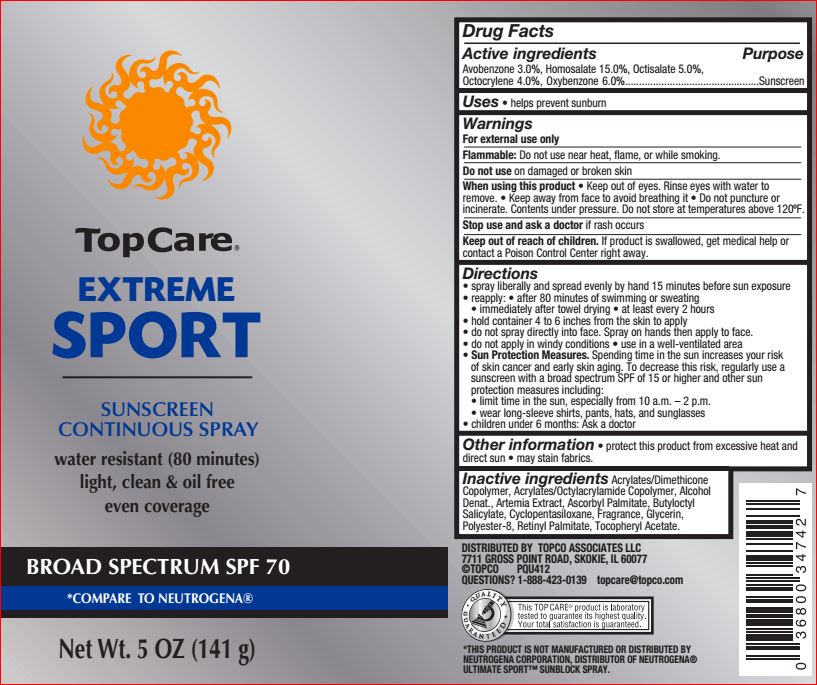 DRUG LABEL: Extreme Sport SPF 70
NDC: 36800-727 | Form: SPRAY
Manufacturer: Top Care
Category: otc | Type: HUMAN OTC DRUG LABEL
Date: 20180717

ACTIVE INGREDIENTS: Avobenzone 3 g/100 g; Homosalate 15 g/100 g; Octisalate 5 g/100 g; Octocrylene 4 g/100 g; Oxybenzone 6 g/100 g
INACTIVE INGREDIENTS: ALCOHOL; BRINE SHRIMP; Ascorbyl Palmitate; Butyloctyl Salicylate; CYCLOMETHICONE 5; Glycerin; POLYESTER-8 (1400 MW, CYANODIPHENYLPROPENOYL CAPPED); VITAMIN A PALMITATE; .ALPHA.-TOCOPHEROL ACETATE

Drug Facts

Active ingredients Purpose

Avobenzone - 3.00% Sunscreen
Homosalate - 15.00% Sunscreen
Octisalate - 5.00% Sunscreen
Octocrylene - 4.00% Sunscreen
Oxybenzone - 6.00% Sunscreen

INDICATIONS AND USAGE

Uses • helps prevent sunburn

Warnings For external use only

Flammable: Do not use near heat, flame, or while smoking

Do not use on damaged or broken skin
When using this product keep out of eyes. Rinse with water to remove. Keep away from face to avoid breathing it. Do not puncture or incinerate. Contents under pressure. Do not store at temperature 120F

Stop use and ask a doctor if rash occurs

Keep out of reach of children. If product is swallowed, get medical help or contact a Poison Control Center right away

Directions

• apply liberally 15 minutes before sun exposure
• reapply: • after 80 minutes of swimming or sweating
• immediately after towel drying • at least every 2 hours
• Sun Protection Measures. Spending time in the sun increases
your risk of skin cancer and early skin aging. To decrease this
risk, regularly use a sunscreen with a broad spectrum SPF of 15
or higher and other sun protection measures including:
• limit time in the sun, especially from 10 a.m. – 2 p.m.
• wear long-sleeve shirts, pants, hats, and sunglasses
• children under 6 months: Ask a doctor

Inactive ingredients

Acrylates/Dimethicone Copolymer, Acrylates/Octylacrylamide Copolymer, Alcohol Denat., Artemia Extract, Ascorbyl Palmitate, Butyloctyl Salicylate, Cyclopentasiloxane, Fragrance, Glycerin, Polyester-8, Retinyl Palmitate, Tocopheryl Acetate